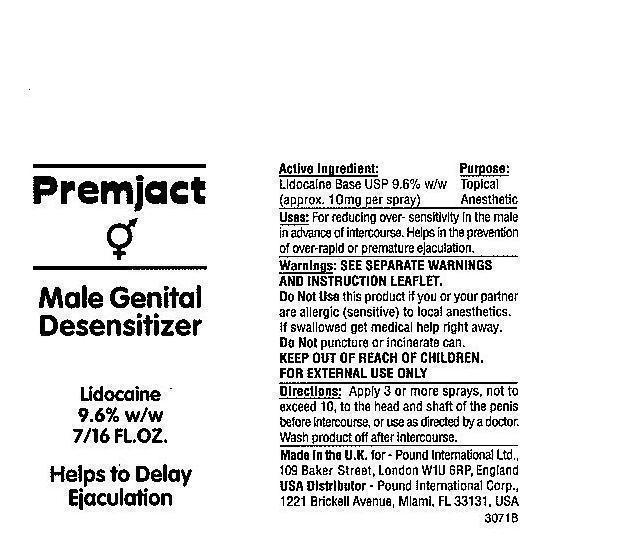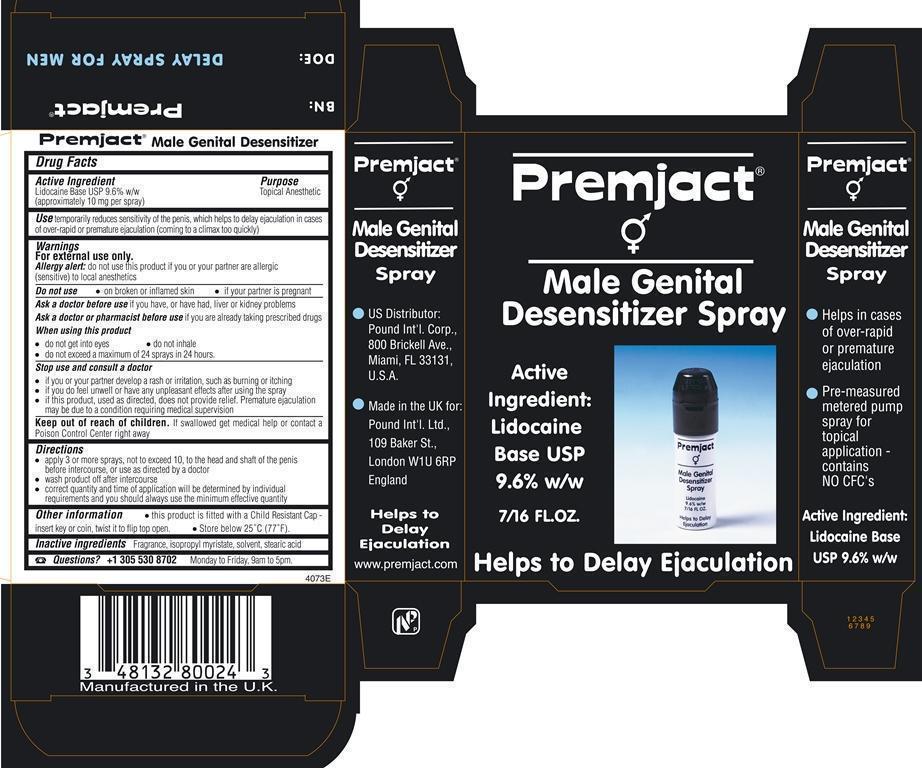 DRUG LABEL: Premjact Male Desensitizer
NDC: 57707-058 | Form: SPRAY, METERED
Manufacturer: Pound International
Category: otc | Type: HUMAN OTC DRUG LABEL
Date: 20190110

ACTIVE INGREDIENTS: LIDOCAINE 9.6 g/100 mL
INACTIVE INGREDIENTS: ISOPROPYL MYRISTATE; STEARIC ACID

Premjact Male Genital Desensitizer Spray

Active Ingredient Purpose

Lidocaine Base USP 9.6% w/w (approximately 10 mg per spray) Topical Analgesic

PURPOSE

Use temporarily reduces sensitivity of the penis, which helps to delay ejaculation in cases of over-rapid or premature ejaculation (coming to a climax too quickly

Keep out of reach of children

Stop use and consult a doctor

- if you or your partner develop a rash or irritation, such as burning or itching
- If you do feel unwell or have any unpleasant effects after using the spray
- if this product, used as directed, does not provide relief. Premature ejaculation may be due to a condition requiring medical supervision.

Warnings

For external use only

Allergy alert: do not use this product if you or your partner are allergic (sensitive) to local anesthetics

Do not use

- on broken or inflamed skin
- if your partner is pregnant

Ask a doctor before use if you have, or ever had, liver or kidney problems

Ask a doctor or pharmacist before use if you are already taking prescribed drugs

When using this product

- do not get into eyes
- do not inhale
- do not exceed a maximum of 24 sprays in 24 hours

directions

- Apply 3 or more sprays, not to exceed 10, to the head and shaft of the penis before intercourse or use as directed by a doctor
- Wash product off after intercourse
- correct quantity and time of application will be determined by individual requirements and you should always use the minimum effective quantity

There are no inactive ingredients

PACKAGE LABEL

Premjact

Male Genital Desensitizer Spray

7/16 Fl.Oz.